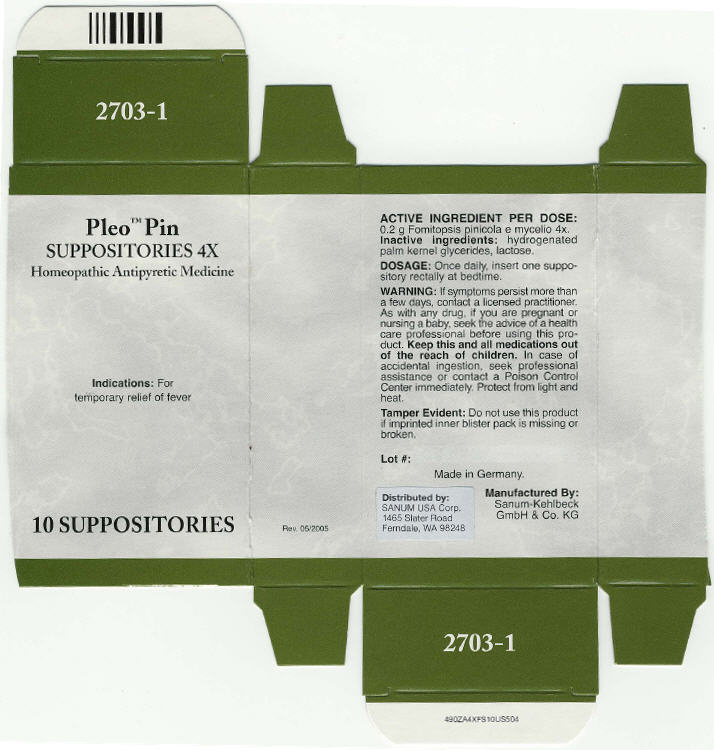 DRUG LABEL: Pleo Pin
NDC: 60681-2703 | Form: SUPPOSITORY
Manufacturer: Sanum Kehlbeck GmbH & Co. KG
Category: homeopathic | Type: HUMAN OTC DRUG LABEL
Date: 20091013

ACTIVE INGREDIENTS: fomitopsis pinicola 4 [hp_X]/1 1
INACTIVE INGREDIENTS: lactose

Pleo™ Pin
SUPPOSITORIES 4X

Homeopathic Antipyretic Medicine

10 SUPPOSITORIES

Indications

For temporary relief of fever

ACTIVE INGREDIENT PER DOSE

0.2 g Fomitopsis pinicola e mycelio 4x.

Inactive ingredients

hydrogenated palm kernel glycerides, lactose.

DOSAGE

Once daily, insert one suppository rectally at bedtime.

WARNING

If symptoms persist more than a few days, contact a licensed practitioner. As with any drug, if you are pregnant or nursing a baby, seek the advice of a health care professional before using this product.

KEEP OUT OF REACH OF CHILDREN

Keep this and all medications out of the reach of children. In case of accidental ingestion, seek professional assistance or contact a Poison Control Center immediately.

STORAGE AND HANDLING

Protect from light and heat.

Tamper Evident

Do not use this product if imprinted inner blister pack is missing or broken.

Made in Germany.

Distributed by:
SANUM USA Corp.
1465 Slater Road
Ferndale, WA 98248

Manufactured By:
Sanum-Kehlbeck
GmbH & Co. KG

Rev. 05/2005

PRINCIPAL DISPLAY PANEL - 10 Suppositories Carton

Pleo™ Pin
SUPPOSITORIES 4X

Homeopathic Antipyretic Medicine

Indications: For
temporary relief of fever

10 SUPPOSITORIES